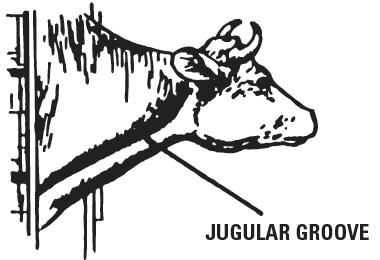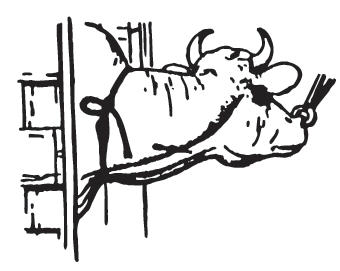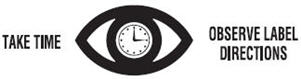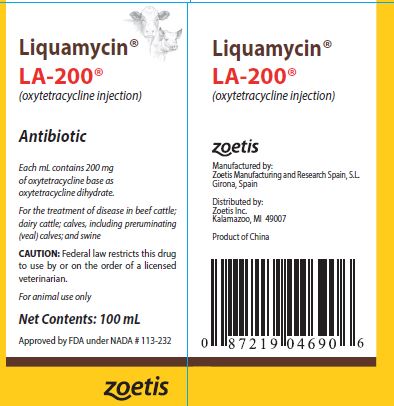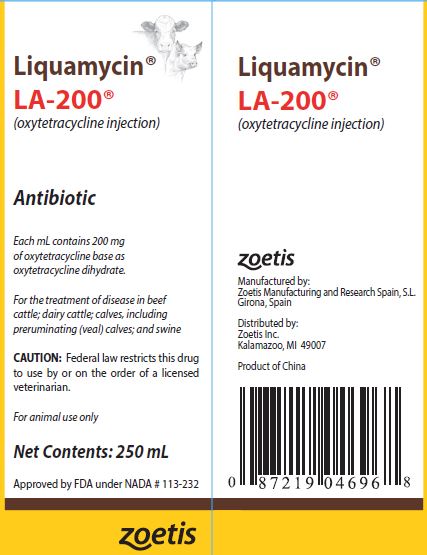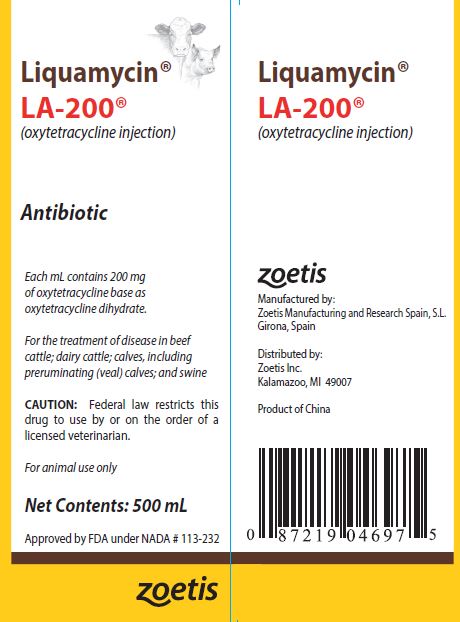 DRUG LABEL: Liquamycin
NDC: 54771-1140 | Form: INJECTION, SOLUTION
Manufacturer: Zoetis Inc.
Category: animal | Type: PRESCRIPTION ANIMAL DRUG LABEL
Date: 20240213

ACTIVE INGREDIENTS: OXYTETRACYCLINE 200 mg/1 mL
INACTIVE INGREDIENTS: PYRROLIDONE; POVIDONE; MAGNESIUM OXIDE; SODIUM FORMALDEHYDE SULFOXYLATE; 2-AMINOETHANOL; HYDROCHLORIC ACID

Liquamycin® LA-200®

Liquamycin® LA-200®
(oxytetracycline injection)
Antibiotic
Each mL contains 200 mg of oxytetracycline base as oxytetracycline dihydrate.
For the treatment of disease in beef cattle; dairy cattle; calves, including preruminating (veal) calves; and swine
CAUTION: Federal law restricts this drug to use by or on the order of a licensed veterinarian.
For animal use only
Read Entire Package Insert Carefully Before Using This Product

DESCRIPTION

Liquamycin LA-200 (oxytetracycline injection) is a sterile, ready-to-use solution for the administration of the broad-spectrum antibiotic oxytetracycline by injection.
Liquamycin LA-200 administered for the treatment of bacterial pneumonia (cattle or swine) or anaplasmosis (cattle) at a dosage of 9 mg of oxytetracycline per lb of body weight has been demonstrated in clinical trials to be as effective as 2 or 3 repeated, daily treatments at 3–5 mg/lb of body weight.
Liquamycin LA-200 does not require refrigeration; however, it is recommended that it be stored at room temperature, 15°– 30°C (59°– 86°F). The antibiotic activity of oxytetracycline is not appreciably diminished in the presence of body fluids, serum, or exudates.

CAUTION

When administered to cattle, muscle discoloration may necessitate trimming of the injection site(s) and surrounding tissues during the dressing procedure.

WARNINGS

Discontinue treatment at least 28 days prior to slaughter of cattle and swine. Milk taken from animals during treatment and for 96 hours after the last treatment must not be used for food. Rapid intravenous administration may result in animal collapse. Oxytetracycline should be administered intravenously slowly over a period of at least 5 minutes.

PRECAUTIONS

Exceeding the highest recommended level of drug per lb of body weight per day, administering more than the recommended number of treatments, and/or exceeding 10 mL intramuscularly or subcutaneously per injection site in adult beef and dairy cattle, and 5 mL intramuscularly per injection site in adult swine, may result in antibiotic residues beyond the withdrawal period.

At the first sign of any adverse reaction, discontinue use of the product and seek the advice of your veterinarian. Some of the reactions may be attributed either to anaphylaxis (an allergic reaction) or to cardiovascular collapse of unknown cause.
Shortly after injection, treated animals may have transient hemoglobinuria resulting in darkened urine.
As with all antibiotic preparations, use of this drug may result in overgrowth of nonsusceptible organisms, including fungi. A lack of response by the treated animal, or the development of new signs, may suggest that an overgrowth of nonsusceptible organisms has occurred. If any of these conditions occur, consult your veterinarian.
Since bacteriostatic drugs may interfere with the bactericidal action of penicillin, it is advisable to avoid giving Liquamycin LA-200 in conjunction with penicillin.

ADVERSE REACTIONS

Reports of adverse reactions associated with oxytetracycline administration include injection site swelling, restlessness, ataxia, trembling, swelling of eyelids, ears, muzzle, anus and vulva (or scrotum and sheath in males), respiratory abnormalities (labored breathing), frothing at the mouth, collapse and possibly death. Some of these reactions may be attributed to anaphylaxis (an allergic reaction) or to cardiovascular collapse of unknown cause.

STORAGE

Store at room temperature 15°– 30°C (59°– 86°F).
Protect from freezing. Use within 28 days of first vial puncture. Stopper may be punctured a maximum of 40 times.

CARE OF SICK ANIMALS

The use of antibiotics in the management of diseases is based on an accurate diagnosis and an adequate course of treatment. When properly used in the treatment of diseases caused by oxytetracycline-susceptible organisms, most animals that have been treated with Liquamycin LA-200 show a noticeable improvement within 24–48 hours.

INDICATIONS

Liquamycin LA-200 is intended for use in the treatment of the following diseases in beef cattle; dairy cattle; calves, including preruminating (veal) calves; and swine when due to oxytetracycline-susceptible organisms:

Cattle

Liquamycin LA-200 is indicated in the treatment of pneumonia and shipping fever complex associated with Pasteurella spp. and Hemophilus spp.; infectious bovine keratoconjunctivitis (pinkeye) caused by Moraxella bovis; foot rot and diphtheria caused by Fusobacterium necrophorum; bacterial enteritis (scours) caused by Escherichia coli; wooden tongue caused by Actinobacillus lignieresii; leptospirosis caused by Leptospira pomona; anaplasmosis caused by Anaplasma marginale; anthrax caused by Bacillus anthracis; and wound infections and acute metritis caused by strains of staphylococci and streptococci organisms sensitive to oxytetracycline.

Swine

Liquamycin LA-200 is indicated in the treatment of bacterial enteritis (scours, colibacillosis) caused by Escherichia coli; pneumonia caused by Pasteurella multocida; and leptospirosis caused by Leptospira pomona.
In sows, Liquamycin LA-200 is indicated as an aid in the control of infectious enteritis (baby pig scours, colibacillosis) in suckling pigs caused by Escherichia coli.

DOSAGE

Cattle

Liquamycin LA-200 is to be administered by intramuscular, subcutaneous, or intravenous injection. Intramuscular administration is not recommended according to Beef Quality Assurance Guidelines.
A single dose of 9 mg of oxytetracycline per lb of body weight administered intramuscularly or subcutaneously is recommended in the treatment of infectious bovine keratoconjunctivitis (pinkeye) caused by Moraxella bovis; and in the treatment of the following conditions where retreatment is impractical due to husbandry conditions, such as cattle on range, or where their repeated restraint is inadvisable: bacterial pneumonia caused by Pasteurella spp. (shipping fever) in calves and yearlings, and anaplasmosis caused by Anaplasma marginale.
Liquamycin LA-200 can also be administered by intravenous, subcutaneous, or intramuscular injection at a level of 3–5 mg of oxytetracycline per lb of body weight per day.
In the treatment of severe foot rot and advanced cases of other indicated diseases, a dosage level of 5 mg/lb of body weight per day is recommended. Treatment should be continued 24–48 hours following remission of disease signs; however, not to exceed a total of 4 consecutive days. Consult your veterinarian if improvement is not noted within 24–48 hours of the beginning of treatment.

Swine

A single dosage of 9 mg of Liquamycin LA-200 per lb of body weight administered intramuscularly in the neck region is recommended in the treatment of bacterial pneumonia caused by Pasteurella multocida in swine, where retreatment is impractical due to husbandry conditions or where repeated restraint is inadvisable.
Liquamycin LA-200 can also be administered by intramuscular injection at a level of 3–5 mg of oxytetracycline per lb of body weight per day. Treatment should be continued 24–48 hours following remission of disease signs; however, not to exceed a total of 4 consecutive days. Consult your veterinarian if improvement is not noted within 24–48 hours of the beginning of treatment.
For sows, administer once intramuscularly in the neck region 3 mg of oxytetracycline per lb of body weight approximately 8 hours before farrowing or immediately after completion of farrowing.
For swine weighing 25 lb of body weight and under, Liquamycin LA-200 should be administered undiluted for treatment at 9 mg/lb but should be administered diluted for treatment at 3 or 5 mg/lb.

 | 9 mg/lb Dosage | 3 or 5 mg/lb Dosage
 | Volume of Undiluted Liquamycin LA-200 | Volume of Diluted Liquamycin LA-200
Body Weight | 9 mg/lb | 3 mg/lb | Dilution [To prepare dilutions, add 1 part Liquamycin LA-200 to 3, 5, or 7 parts of sterile water, or 5% dextrose solution as indicated; the diluted product should be used immediately.] | 5 mg/lb
5 lb | 0.2 mL | 0.6 mL | 1:7 | 1.0 mL
10 lb | 0.5 mL | 0.9 mL | 1:5 | 1.5 mL
25 lb | 1.1 mL | 1.5 mL | 1:3 | 2.5 mL

*To prepare dilutions, add 1 part Liquamycin LA-200 to 3, 5, or 7 parts of sterile water, or 5% dextrose solution as indicated; the diluted product should be used immediately.

DIRECTIONS FOR USE

Liquamycin LA-200 is intended for use in the treatment of disease due to oxytetracycline-susceptible organisms in beef cattle; dairy cattle; calves, including preruminating (veal) calves; and swine. A thoroughly cleaned, sterile needle and syringe should be used for each injection (needles and syringes may be sterilized by boiling in water for 15 minutes). In cold weather, Liquamycin LA-200 should be warmed to room temperature before administration to animals. Before withdrawing the solution from the bottle, disinfect the rubber cap on the bottle with suitable disinfectant, such as 70% alcohol. The injection site should be similarly cleaned with the disinfectant. Needles of 16–18 gauge and 1–1½ inches long are adequate for intramuscular and subcutaneous injections. Needles 2–3 inches are recommended for intravenous use.

Intramuscular Administration

Intramuscular injections should be made by directing the needle of suitable gauge and length into the fleshy part of a thick muscle in the neck region; avoid blood vessels and major nerves. Before injecting the solution, pull back gently on the plunger. If blood appears in the syringe, a blood vessel has been entered; withdraw the needle and select a different site. In cattle, intramuscular administration is not recommended according to Beef Quality Assurance Guidelines. No more than 10 mL should be injected intramuscularly at any one site in adult beef and dairy cattle, and not more than 5 mL per site in adult swine; rotate injection sites for each succeeding treatment. The volume administered per injection site should be reduced according to age and body size so that 1-2 mL per site is injected in small calves.

Subcutaneous Administration

Subcutaneous injections in beef cattle, dairy cattle, and calves, including preruminating (veal) calves, should be made by directing the needle of suitable gauge and length through the loose folds of the neck skin in front of the shoulder. Care should be taken to ensure that the tip of the needle has penetrated the skin but is not lodged in muscle. Before injecting the solution, pull back gently on the plunger. If blood appears in the syringe, a blood vessel has been entered; withdraw the needle and select a different site. The solution should be injected slowly into the area between the skin and muscles. No more than 10 mL should be injected subcutaneously at any one site in adult beef and dairy cattle; rotate injection sites for each succeeding treatment. The volume administered per injection site should be reduced according to age and body size so that 1–2 mL per site is injected in small calves.

Intravenous Administration

Liquamycin LA-200 may be administered intravenously to beef and dairy cattle. As with all highly concentrated materials, Liquamycin LA-200 should be administered slowly by the intravenous route.

Preparation of the Animal for Injection

1. Approximate location of vein. The jugular vein runs in the jugular groove on each side of the neck from the angle of the jaw to just above the brisket and slightly above and to the side of the windpipe (see Fig. I).
2. Restraint. A stanchion or chute is ideal for restraining the animal. With a halter, rope, or cattle leader (nose tongs), pull the animal's head around the side of the stanchion, cattle chute, or post in such a manner to form a bow in the neck (see Fig. II), then snub the head securely to prevent movement. By forming the bow in the neck, the outside curvature of the bow tends to expose the jugular vein and make it easily accessible.
  Caution: Avoid restraining the animal with a tight rope or halter around the throat or upper neck which might impede blood flow. Animals that are down present no problem so far as restraint is concerned.
3. Clip hair in area where injection is to be made (over the vein in the upper third of the neck). Clean and disinfect the skin with alcohol or other suitable antiseptic.

FIGURE I

FIGURE II

Entering the Vein and Making the Injection

1. Raise the vein. This is accomplished by tying the choke rope tightly around the neck close to the shoulder. The rope should be tied in such a way that it will not come loose and so that it can be untied quickly by pulling the loose end (see Fig. II). In thick-necked animals, a block of wood placed in the jugular groove between the rope and the hide will help considerably in applying the desired pressure at the right point. The vein is a soft flexible tube through which blood flows back to the heart. Under ordinary conditions it cannot be seen or felt with the fingers. When the flow of blood is blocked at the base of the neck by the choke rope, the vein becomes enlarged and rigid because of the back pressure. If the choke rope is sufficiently tight, the vein stands out and can be easily seen and felt in thin-necked animals. As a further check in identifying the vein, tap it with the fingers in front of the choke rope. Pulsations that can be seen or felt with the fingers in front of the point being tapped will confirm the fact that the vein is properly distended. It is impossible to put the needle into the vein unless it is distended. Experienced operators are able to raise the vein simply by hand pressure, but the use of a choke rope is more certain.

2. Inserting the needle. This involves 3 distinct steps. First, insert the needle through the hide. Second, insert the needle into the vein. This may require 2 or 3 attempts before the vein is entered. The vein has a tendency to roll away from the point of the needle, especially if the needle is not sharp. The vein can be steadied with the thumb and finger of one hand. With the other hand, the needle point is placed directly over the vein, slanting it so that its direction is along the length of the vein, either toward the head or toward the heart. Properly positioned this way, a quick thrust of the needle will be followed by a spurt of blood through the needle, which indicates that the vein has been entered. Third, once in the vein, the needle should be inserted along the length of the vein all the way to the hub, exercising caution to see that the needle does not penetrate the opposite side of the vein. Continuous steady flow of blood through the needle indicates that the needle is still in the vein. If blood does not flow continuously, the needle is out of the vein (or clogged) and another attempt must be made. If difficulty is encountered, it may be advisable to use the vein on the other side of the neck.

3. While the needle is being placed in proper position in the vein, an assistant should get the medication ready so that the injection can be started without delay after the vein has been entered.

4. Making the injection. With the needle in position as indicated by continuous flow of blood, release the choke rope by a quick pull on the free end. This is essential—the medication cannot flow into the vein while it is blocked. Immediately connect the syringe containing Liquamycin LA-200 to the needle and slowly depress the plunger. If there is resistance to depression of the plunger, this indicates that the needle has slipped out of the vein (or is clogged) and the procedure will have to be repeated. Watch for any swelling under the skin near the needle, which would indicate that the medication is not going into the vein. Should this occur, it is best to try the vein on the opposite side of the neck.

5. Removing the needle. When injection is complete, remove needle with straight pull. Then apply pressure over area of injection momentarily to control any bleeding through needle puncture, using cotton soaked in alcohol or other suitable antiseptic.

Not For Human Use
Approved by FDA under NADA # 113-232

Distributed by:
Zoetis Inc.
Kalamazoo, MI 49007

Revised: October 2022

40039386

PRINCIPAL DISPLAY PANEL - 100 mL Carton Label

40039384

PRINCIPAL DISPLAY PANEL - 250 mL Carton Label

40039387

PRINCIPAL DISPLAY PANEL - 500 mL Carton Label

40039389